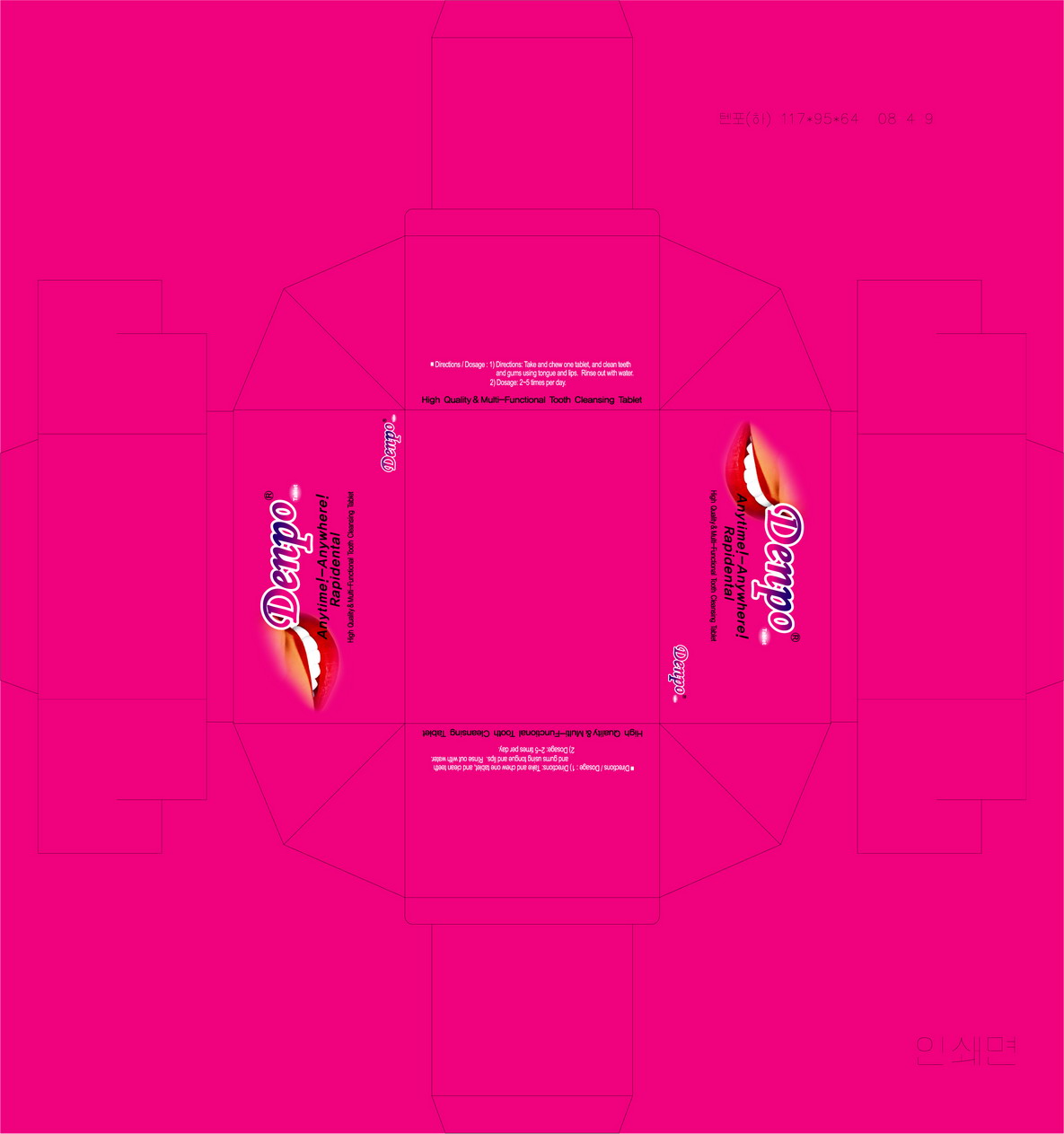 DRUG LABEL: Denpo
NDC: 52146-1001 | Form: TABLET, CHEWABLE
Manufacturer: Suheung Capsule Co., Ltd
Category: otc | Type: HUMAN OTC DRUG LABEL
Date: 20100318

ACTIVE INGREDIENTS: SODIUM FLUORIDE 1.1 mg/1 1

Drug Facts

Active ingredient: Sodium Fluoride

DESCRIPTION

Benefits / Effects
(1) cavity prevention
(2) removal of bad breath, cleaning of oral cavity
Directions / dosage
(1) direction
take and chew one tablet, and clean teeth and gums using tongue and lips, rinse out with water
(2) dosage
2~5 times per day
Caution
(1) avoid direct sunlight, store in a cool dry place
(2) do not swallow
Warning
(1) the fluoride content of this product is 597.46 ppm (total fluoride content needs to be below 1,000 ppm)
(2) for children under six, use a pea-sized amount per use, do not eat or swallow
(3) immediately contact a physician if a child under six has swallowed a large portion
(4) keep and store away from children under six